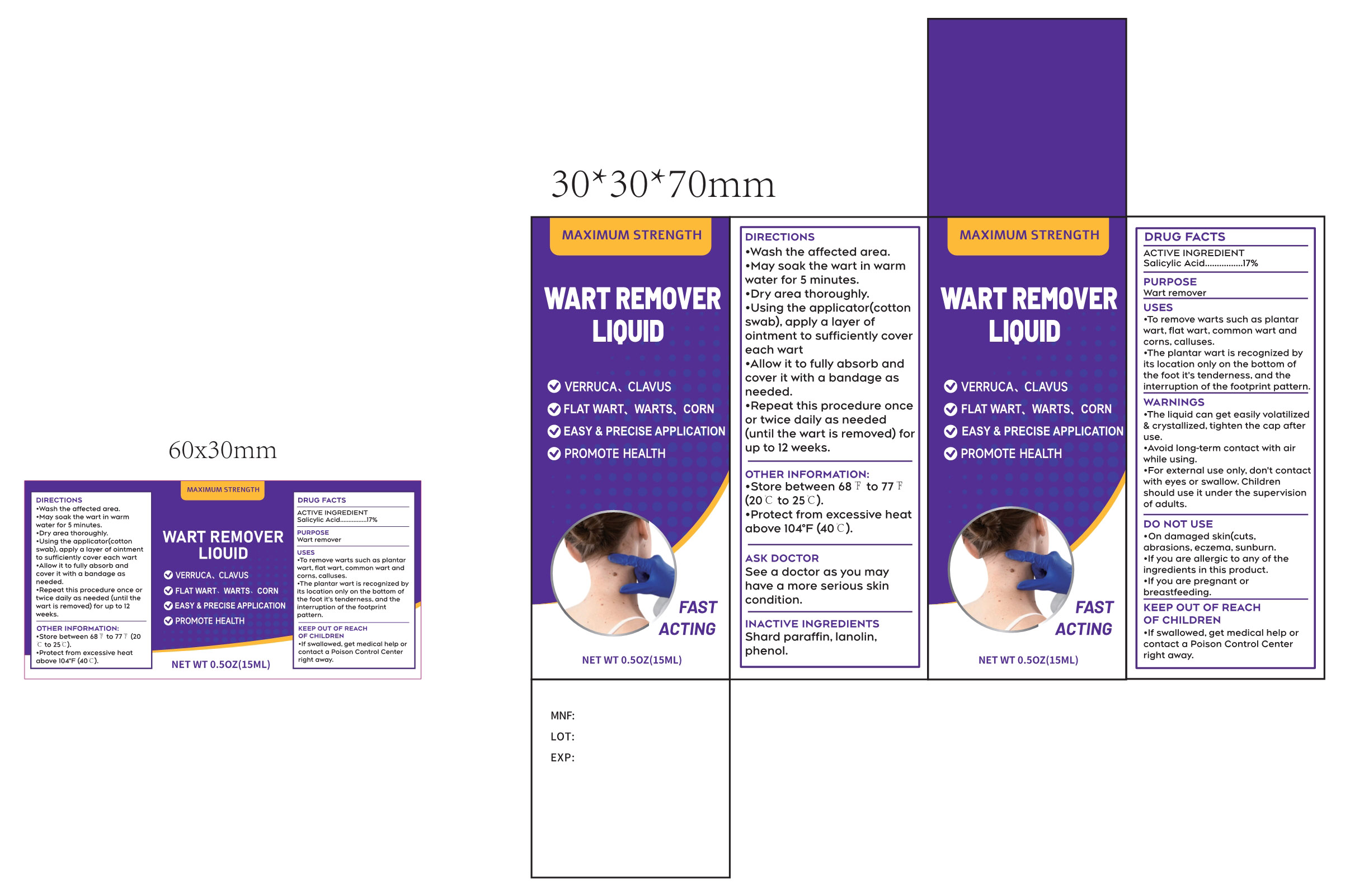 DRUG LABEL: WART REMOVER
NDC: 87255-003 | Form: LIQUID
Manufacturer: Shenzhen Mengyue Technology Co., Ltd.
Category: otc | Type: HUMAN OTC DRUG LABEL
Date: 20251113

ACTIVE INGREDIENTS: SALICYLIC ACID 17 g/100 mL
INACTIVE INGREDIENTS: PHENOL; LANOLIN; PARAFFIN

003 WART REMOVER LIQUID

ACTIVE INGREDIENT

Salicylic Acid 17%

PURPOSE

Wart remover

USES
•To remove warts such as plantar wart, flat wart, common wart and corns, calluses.
•The plantar wart is recognized by its location only on the bottom of the foot it's tenderness, and the interruption of the footprint pattern.

WARNINGS

· The liquid can get easily volatilized & crystallized, tighten the cap after use.

· Avoid long-term contact with air while using.

· For external use only, don't contact with eyes or swallow.Children should use it under the supervision of adults.

DO NOT USE

• On damaged skin(cuts, abrasions, eczema, sunburn.

• If you are allergic to any of the ingredients in this product.

• If you are pregnant or breastfeeding.

WHEN USING

N/A

ASK DOCTOR

See a doctor as you may have a more serious skin condition.

KEEP OUT OF REACHOF CHILDREN

•If swallowed, get medical help or contact a Poison Control Center right away.

DIRECTIONS

• Wash the affected area.

• May soak the wart in warm water for 5 minutes.

• Dry area thoroughly.

• Using the applicator(cotton swab),apply a layer of ointment to sufficiently cover each wart

• Allow it to fully absorb and cover it with a bandage as needed.

• Repeat this procedure once or twice daily as needed(until the wart is removed) for up to 12 weeks.

OTHER INFORMATION:

• Store between 68°F to 77°F(20°C to 25°C).

• Protect from excessive heat above 104°F(40°C).

INACTIVE INGREDIENTS
Shard paraffin, lanolin, phenol.